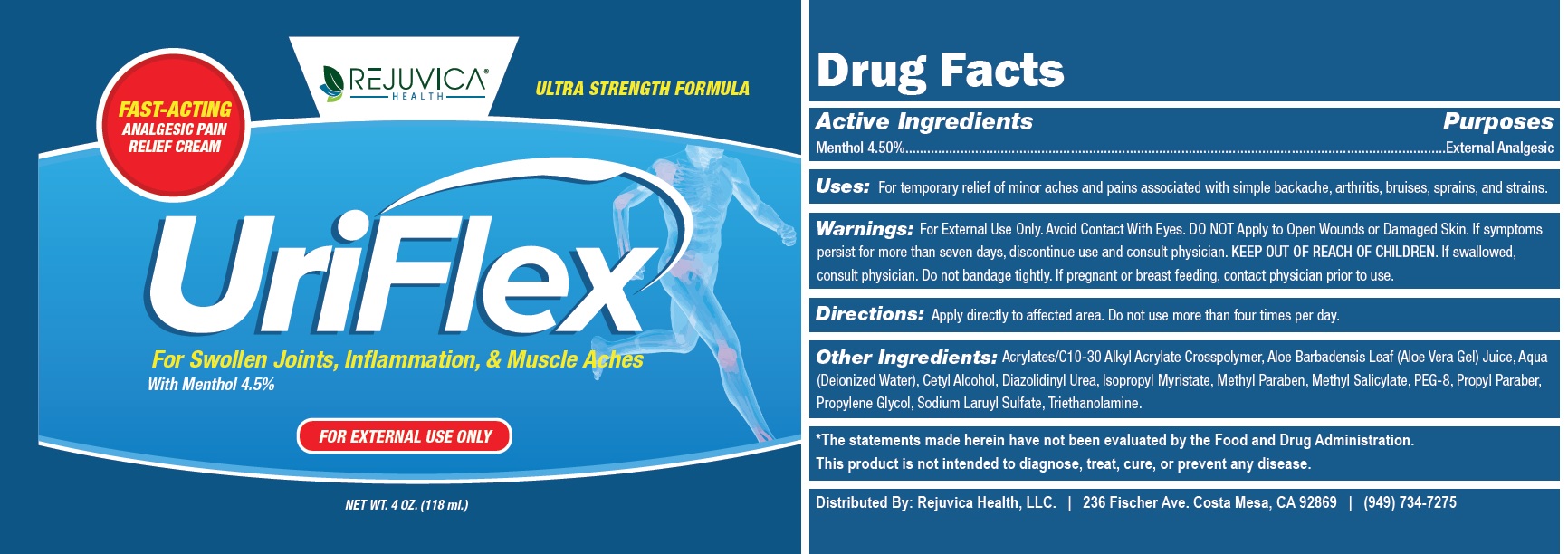 DRUG LABEL: URIFLEX Fast Acting Analgesic Pain Relief
NDC: 73168-004 | Form: CREAM
Manufacturer: Rejuvica LLC
Category: otc | Type: HUMAN OTC DRUG LABEL
Date: 20231105

ACTIVE INGREDIENTS: MENTHOL 45 mg/1 mL
INACTIVE INGREDIENTS: CARBOMER INTERPOLYMER TYPE A (ALLYL SUCROSE CROSSLINKED); ALOE VERA LEAF; WATER; CETYL ALCOHOL; DIAZOLIDINYL UREA; ISOPROPYL MYRISTATE; METHYLPARABEN; METHYL SALICYLATE; POLYETHYLENE GLYCOL 400; PROPYLPARABEN; PROPYLENE GLYCOL; SODIUM LAURYL SULFATE; TROLAMINE

URIFLEX Fast Acting Analgesic Pain Relief Cream

Active Ingredients

Menthol 4.50%

Purposes

External Analgesic

Uses:

For temporary relief of minor aches and pains associated with simple backache, arthritis, bruises, sprains, and strains.

Warnings:

For External Use Only. Avoid Contact With Eyes.

DO NOT Apply

to Open Wounds or Damaged Skin. If symptoms persist for more than seven days, discontinue use and consult physician.

KEEP OUT OF REACH OF CHILDREN.

If swallowed, consult physician. Do not bandage tightly.

If pregnant or breast feeding,

contact physician prior to use.

Directions:

Apply directly to affected area. Do not use more than four times per day.

Other Ingredients:

Acrylates/C10-30 Alkyl Acrylate Crosspolymer, Aloe Barbadensis Leaf (Aloe Vera Gel) Juice, Aqua (Deionized Water), Cetyl Alcohol, Diazolidinyl Urea, Isopropyl Myristate, Methyl Paraben, Methyl Salicylate, PEG-8, Propyl Paraber, Propylene Glycol, Sodium Laruyl Sulfate, Triethanolamine.